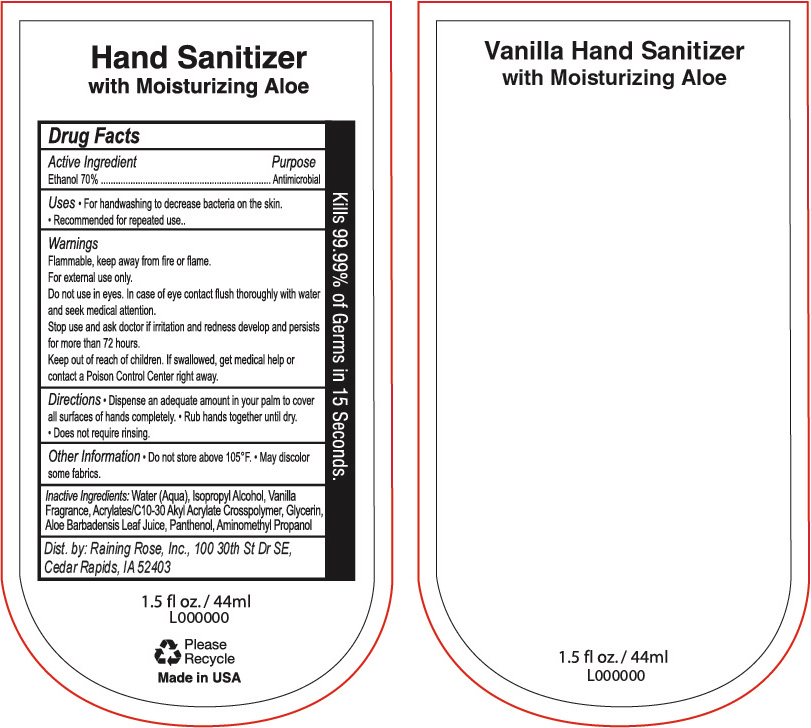 DRUG LABEL: Hand Sanitizer
NDC: 65692-2063 | Form: GEL
Manufacturer: Raining Rose, INC
Category: otc | Type: HUMAN OTC DRUG LABEL
Date: 20210226

ACTIVE INGREDIENTS: ALCOHOL 70 mL/100 mL
INACTIVE INGREDIENTS: ISOPROPYL ALCOHOL; CARBOMER INTERPOLYMER TYPE A (ALLYL SUCROSE CROSSLINKED); ALOE VERA LEAF; PANTHENOL; AMINOMETHYLPROPANOL (PERFLUORO-C6-C12 ETHYL)PHOSPHATE; WATER; GLYCERIN

ACTIVE INGREDIENT

Ethanol 70%

PURPOSE

Antimicrobial

INDICATIONS AND USAGE

For handwashing to decrease bacteria on the skin. Recommended for repeated use.

WARNINGS

Flammable, keep away from fire or flame. For external use only. Do not use in eyes. In case of eye contact flush thoroughly with water and seek medical attention. Stop use and ask doctor if irritation and redness develop and persists for more than 72 hours. If swallowed, get medical help or contact a Poison Control Center right away.

Keep out of reach of children.

DOSAGE AND ADMINISTRATION

- Dispense an adequate amount in your palm to cover all surfaces of hands completely
- Rub hands together until dry
- Does not require rinsing.

OTHER SAFETY INFORMATION

- Do not store above 105*
- May discolor some fabrics

INACTIVE INGREDIENT

Water (Aqua), Isopropyl Alcohol, Vanilla Fragrance, Acylates/C10-30 Akyl Acrylate Crosspolymer, Glycerin, Aloe Barbadensis Leaf Juice, Panthenol, Aminomethyl Propanol.